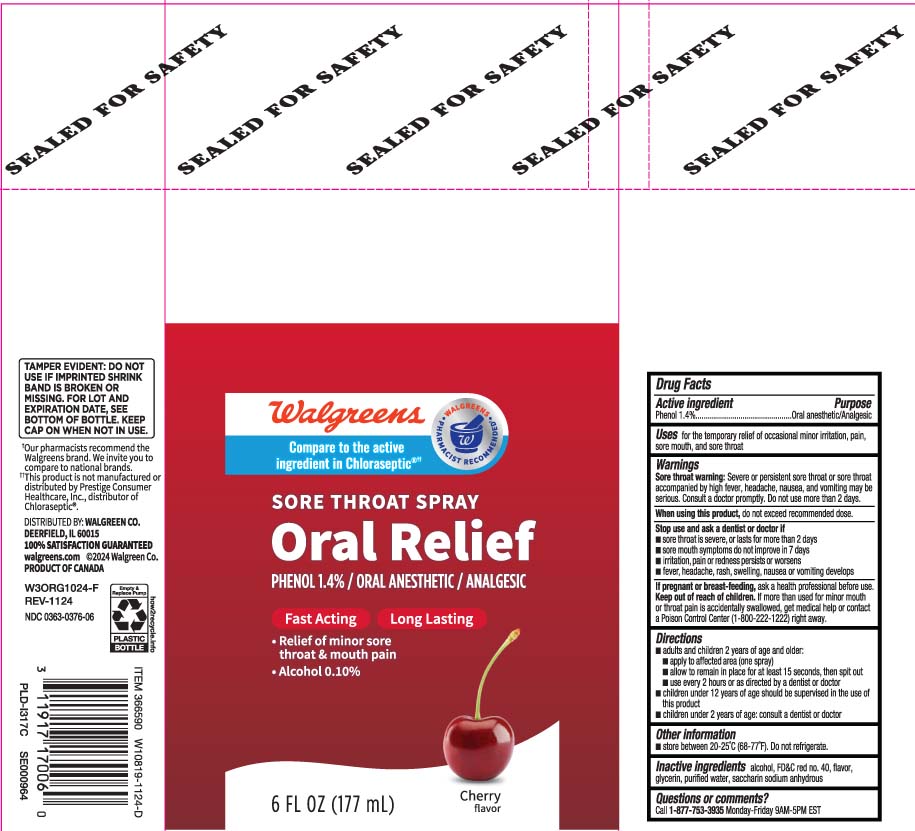 DRUG LABEL: Sore throat
NDC: 0363-0376 | Form: SPRAY
Manufacturer: Walgreens
Category: otc | Type: HUMAN OTC DRUG LABEL
Date: 20241202

ACTIVE INGREDIENTS: PHENOL 1.4 g/100 mL
INACTIVE INGREDIENTS: ALCOHOL; FD&C RED NO. 40; GLYCERIN; WATER; SACCHARIN SODIUM

Drug Facts

Active ingredient

Phenol 1.4%

Purpose

Oral Anesthetic/Analgesic

Uses

for the temporarily relief of occasional minor irritation, pain, sore mouth, and sore throat

Warnings

Sore throat warning: Severe or persistent sore throat or sore throat accompanied by high fever, headache, nausea, and vomiting may be serious. Consult a doctor promptly. Do not use more than 2 days.

When using this product,

do not exceed recommended dose.

Stop use and ask a dentist or doctor if

- sore throat is severe,or lasts for more than 2 days
- sore mouth symptoms do not improve in 7 days
- irritation, pain or redness persists or worsen
- fever, headache, rash, swelling, nausea or vomiting develops

If pregnant or breast-feeding,

ask a health professional before use.

Keep out of reach of children.

If more than used for minor mouth or throat pain is accidentally swallowed, get medical help or contact a Poison Control Center (1-800-222-1222) right away.

Directions

- adults and children 2 years of age and older
  - apply to affected area (one spray)
  - allow to remain in place for at least 15 seconds, then spit out
  - use every 2 hours as directed by a dentist or doctor
- children under 12 years of age should be supervised in the use of this product
- children under 2 years of age, consult a dentist or doctor

Other information

- store between 20-25ºC (68-77ºF). Do not refrigerate.

Inactive ingredients

alcohol, FD&C red #40, flavor, glycerin, purified water, saccharin sodium anhydrous

Questions or comments?

Call 1-877-753-3935 Monday-Friday 9AM-5PM EST

Principal Display Panel

Compare to the active ingredient in Chloraseptic®††

SORE THROAT SPRAY

Oral Relief

PHENOL 1.4% / ORAL ANESTHETIC / ANALGESIC

Fast Acting Long Lasting

- Relief of minor sore throat & mouth pain
- Alcohol 0.10%

CHERRY FLAVOR

FL OZ (mL)

TAMPER EVIDENT: DO NOT USE IF IMPRINTED SHRINK BAND IS BROKEN OR MISSING. FOR LOT AND EXPIRATION DATE SEE BOTTOM OF BOTTLE KEEP CAP ON WHEN NOT IN USE.

††This product is not manufactured or distributed by Prestige Consumer Healthcare Inc., distributor of Chloraseptic®.

DISTRIBUTED BY: WALGREEN CO.

DEERFIELD, IL 60015

Package Label

WALGREENS Sore Throat Spray Cherry Flavor